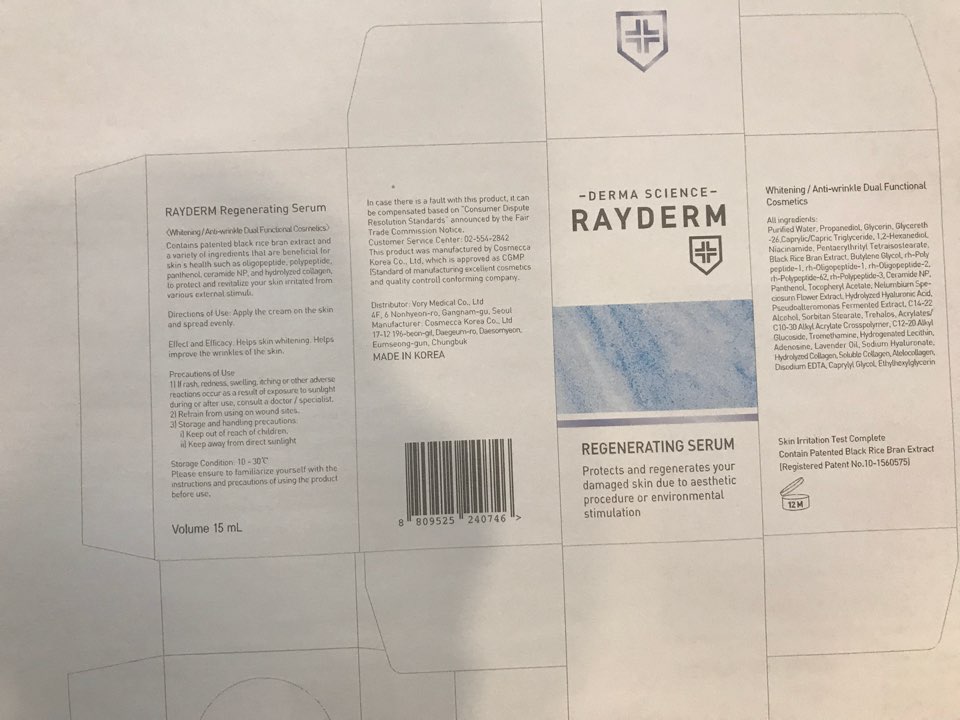 DRUG LABEL: Rayderm Re-generating serum
NDC: 72543-003 | Form: LOTION
Manufacturer: VORY MEDICAL. Inc
Category: otc | Type: HUMAN OTC DRUG LABEL
Date: 20181011

ACTIVE INGREDIENTS: glycerin 1.45 g/15 mL
INACTIVE INGREDIENTS: water; PROPANEDIOL; GLYCERETH-26 CAPRYLATE; 1,2-HEXANEDIOL; NIACINAMIDE; C14-22 ALCOHOLS; PANTHENOL; TREHALOSE; C12-20 ALKYL GLUCOSIDE; TROMETHAMINE; CERAMIDE NP; BUTYLENE GLYCOL; ETHYLHEXYLGLYCERIN; NELUMBO NUCIFERA FLOWER; ADENOSINE; CAPRYLYL GLYCOL

ACTIVE INGREDIENT

Glycerin (9.703%) - Skin Protectact

INACTIVE INGREDIENT

Purified Water, Propanediol, Pentylene Glycol, Caprylic/Capric Triglyceride, Rosehip Fruit Oil, Niacinamide, Black Rice Bran Extract, Butylene Glycol, rh-Polypeptide-1, rh-Oligopeptide-1, rh-Oligopeptide-2, rh-Polypeptide-62, rh-Polypeptide-3, Ceramide NP, Panthenol, Tocopheryl Acetate, Nelumbium Speciosum Flower Extract, Hydrolyzed Hyaluronic Acid, Pseudoalteromonas Fermented Extract, Hydroxyethyl Acrylate/Sodium Acryloyldimethyl Taurate Copolymer, Cetearyl Olivate, Sorbitan Olivate, Hydrogenated Lecithin, Adenosine, Sodium Hyaluronate, Caprylyl Glycol, 1,2-Hexanediol

PURPOSE

Skin Protectact

WARNINGS

Precautions of Use
1) If rash, redness, swelling, itching or other adverse reactions occur as a result of exposure to sunlight during or after use, consult a doctor / specialist.
2) Refrain from using on wound sites.

INDICATIONS & USAGE

Apply the cream on the skin and spread evenly.

DOSAGE & ADMINISTRATION

Apply the cream on the skin and spread evenly.